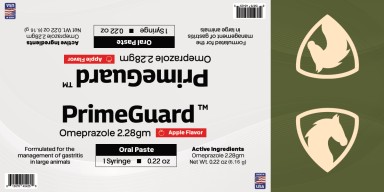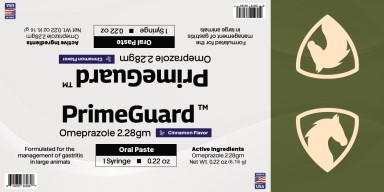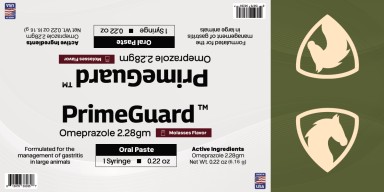 DRUG LABEL: PrimeGuard
NDC: 86213-221 | Form: PASTE
Manufacturer: Vetr, LLC
Category: animal | Type: OTC ANIMAL DRUG LABEL
Date: 20260126

ACTIVE INGREDIENTS: OMEPRAZOLE 0.37 g/1 g
INACTIVE INGREDIENTS: GLYCERIN; SODIUM ALGINATE; SODIUM BICARBONATE; WATER

Vetr PrimeGuard (37% omeprazole oral paste)

WARNINGS AND PRECAUTIONS

Not for use in humans. Keep this and all medications out of the reach of children. In case of ingestion by humans, contact a physician. Do not use in horses intended for human consumption. PrimeGuard is intended for use in healthy horses. If you notice any signs of illness prior to or during the use of this product, consult your veterinarian for appropriate diagnosis and treatment recommendations.

INSTRUCTIONS FOR USE

The minimum recommended dosage is 1 mg/kg per day (0.45 mg/lb) or 1/4 syringe. Each syringe contains 4 individual daily doses for horses weighing 600-1200 lbs. Please refer to this dosage chart for help in determining the correct dose for your horse:

Horse Weight Dose*

<600 lbs Consult your veterinarian

600-1200 lbs 1 dose per day

>1200 lbs 2 doses, once per day

*Dosage duration: 8 or 28 days. Consult your veterinarian.

STORAGE AND HANDLING

Store at 68°F-77°F (20-25°C). For transport, brief periods between 59°F-86°F (15-30°C) are permitted.

ACTIVE INGREDIENT

Omeprazole USP 2.28g per syringe (37% omeprazole)